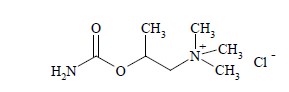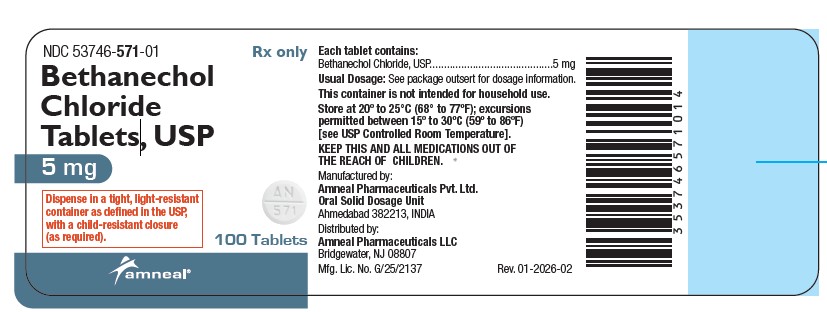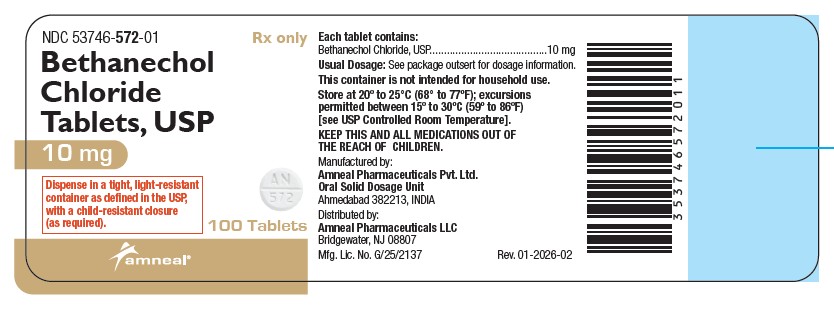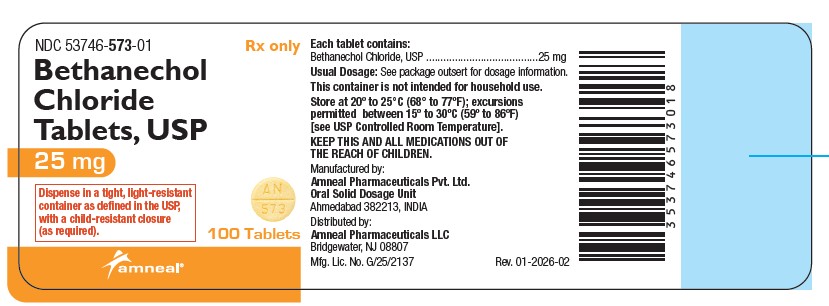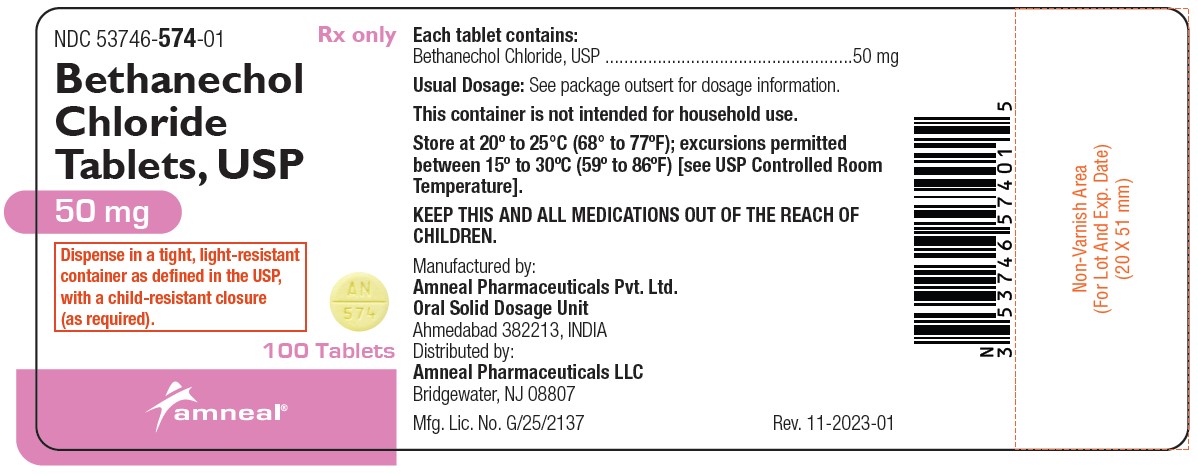 DRUG LABEL: Bethanechol Chloride
NDC: 53746-571 | Form: TABLET
Manufacturer: Amneal Pharmaceuticals of New York LLC
Category: prescription | Type: HUMAN PRESCRIPTION DRUG LABEL
Date: 20260129

ACTIVE INGREDIENTS: BETHANECHOL CHLORIDE 5 mg/1 1
INACTIVE INGREDIENTS: ANHYDROUS LACTOSE; SILICON DIOXIDE; MAGNESIUM STEARATE; CELLULOSE, MICROCRYSTALLINE; SODIUM STARCH GLYCOLATE TYPE A POTATO

Bethanechol Chloride Tablets, USP
(5 mg, 10 mg, 25 mg and 50 mg)
Rx only

DESCRIPTION

Bethanechol chloride, a cholinergic agent, is a synthetic ester which is structurally and pharmacologically related to acetylcholine.

It is designated chemically as 2-[(aminocarbonyl) oxy]-N, N, N-trimethyl-1-propanaminium chloride. Its molecular formula is C7H17CIN2O2 and its structural formula is:

Bethanechol chloride, USP is a white, hygroscopic crystalline powder having a slight amine-like odor, freely soluble in water, and has a molecular weight of 196.68.

Each tablet for oral administration contains 5 mg, 10 mg, 25 mg or 50 mg bethanechol chloride, USP. Bethanechol chloride Tablets, USP also contain the following inactive ingredients: anhydrous lactose, colloidal silicon dioxide, magnesium stearate, microcrystalline cellulose and sodium starch glycolate, Type A. The 25 mg and 50 mg tablets also contain D&C Yellow No.10 Aluminum Lake and FD&C Yellow No. 6 Aluminum Lake.

CLINICAL PHARMACOLOGY

Bethanechol chloride acts principally by producing the effects of stimulation of the parasympathetic nervous system. It increases the tone of the detrusor urinae muscle, usually producing a contraction sufficiently strong to initiate micturition and empty the bladder. It stimulates gastric motility, increases gastric tone and often restores impaired rhythmic peristalsis.

Stimulation of the parasympathetic nervous system releases acetylcholine at the nerve endings. When spontaneous stimulation is reduced and therapeutic intervention is required, acetylcholine can be given, but it is rapidly hydrolyzed by cholinesterase and its effects are transient. Bethanechol chloride is not destroyed by cholinesterase and its effects are more prolonged than those of acetylcholine.

Effects on the GI and urinary tracts sometimes appear within 30 minutes after oral administration of bethanechol chloride, but more often 60 to 90 minutes are required to reach maximum effectiveness. Following oral administration, the usual duration of action of bethanechol chloride is one hour, although large doses (300 mg to 400 mg) have been reported to produce effects for up to six hours. Subcutaneous injection produces a more intense action on bladder muscle than does oral administration of the drug.

Because of the selective action of bethanechol chloride, nicotinic symptoms of cholinergic stimulation are usually absent or minimal when orally or subcutaneously administered in therapeutic doses, while muscarinic effects are prominent. Muscarinic effects usually occur within 5 to 15 minutes after subcutaneous injection, reach a maximum in 15 to 30 minutes, and disappear within two hours. Doses that stimulate micturition and defecation and increase peristalsis do not ordinarily stimulate ganglia or voluntary muscles. Therapeutic test doses in normal human subjects have little effect on heart rate, blood pressure or peripheral circulation.

Bethanechol chloride does not cross the blood-brain barrier because of its charged quaternary amine moiety. The metabolic rate and mode of excretion of the drug have not been elucidated.

A clinical study (Diokno, A.C.; Lapides, J.; Urol 10: 23 to 24, July 1977) was conducted on the relative effectiveness of oral and subcutaneous doses of bethanechol chloride on the stretch response of bladder muscle in patients with urinary retention. Results showed that 5 mg of the drug given subcutaneously stimulated a response that was more rapid in onset and of larger magnitude than an oral dose of 50 mg, 100 mg, or 200 mg. All the oral doses, however, had a longer duration of effect than the subcutaneous dose. Although the 50 mg oral dose caused little change in intravesical pressure in this study, this dose has been found in other studies to be clinically effective in the rehabilitation of patients with decompensated bladders.

INDICATIONS AND USAGE

Bethanechol chloride tablets are indicated for the treatment of acute postoperative and postpartum nonobstructive (functional) urinary retention and for neurogenic atony of the urinary bladder with retention.

CONTRAINDICATIONS

Hypersensitivity to bethanechol chloride, hyperthyroidism, peptic ulcer, latent or active bronchial asthma, pronounced bradycardia or hypotension, vasomotor instability, coronary artery disease, epilepsy and parkinsonism.

Bethanechol chloride should not be employed when the strength or integrity of the gastrointestinal or bladder wall is in question, or in the presence of mechanical obstruction; when increased muscular activity of the gastrointestinal tract or urinary bladder might prove harmful, as following recent urinary bladder surgery, gastrointestinal resection and anastomosis, or when there is possible gastrointestinal obstruction; in bladder neck obstruction, spastic gastrointestinal disturbances, acute inflammatory lesions of the gastrointestinal tract, or peritonitis; or in marked vagotonia.

PRECAUTIONS

General

In urinary retention, if the sphincter fails to relax as bethanechol chloride contracts the bladder, urine may be forced up the ureter into the kidney pelvis. If there is bacteriuria, this may cause reflux infection.

Information for Patients

Bethanechol chloride tablets should preferably be taken one hour before or two hours after meals to avoid nausea or vomiting. Dizziness, lightheadedness or fainting may occur, especially when getting up from a lying or sitting position.

Drug Interactions

Special care is required if this drug is given to patients receiving ganglion blocking compounds because a critical fall in blood pressure may occur. Usually, severe abdominal symptoms appear before there is such a fall in the blood pressure.

Carcinogenesis, Mutagenesis, Impairment of Fertility

Long-term studies in animals have not been performed to evaluate the effects upon fertility, mutagenic or carcinogenic potential of bethanechol chloride.

Pregnancy

Teratogenic Effects

Pregnancy Category C

Animal reproduction studies have not been conducted with bethanechol chloride. It is also not known whether bethanechol chloride can cause fetal harm when administered to a pregnant woman or can affect reproduction capacity. Bethanechol chloride should be given to a pregnant woman only if clearly needed.

Nursing Mothers

It is not known whether this drug is secreted in human milk. Because many drugs are secreted in human milk and because of the potential for serious adverse reactions from bethanechol chloride in nursing infants, a decision should be made whether to discontinue nursing or to discontinue the drug, taking into account the importance of the drug to the mother.

Pediatric Use

Safety and effectiveness in pediatric patients have not been established.

ADVERSE REACTIONS

Adverse reactions are rare following oral administration of bethanechol chloride, but are more common following subcutaneous injection. Adverse reactions are more likely to occur when dosage is increased.

The following adverse reactions have been observed:

Body as a Whole: malaise

Digestive: abdominal cramps or discomfort, colicky pain, nausea and belching, diarrhea, borborygmi, salivation

Renal: urinary urgency

Nervous System: headache

Cardiovascular: a fall in blood pressure with reflex tachycardia, vasomotor response

Skin: flushing producing a feeling of warmth, sensation of heat about the face, sweating

Respiratory: bronchial constriction, asthmatic attacks

Special Senses: lacrimation, miosis

Causal Relationship Unknown: The following adverse reactions have been reported, and a causal relationship to therapy with bethanechol chloride has not been established:

Body as a Whole: malaise

Nervous System: seizures

To report SUSPECTED ADVERSE REACTIONS, contact Amneal Pharmaceuticals at 1-877-835-5472 or FDA at 1-800-FDA-1088 or www.fda.gov/medwatch.

OVERDOSAGE

Early signs of overdosage are abdominal discomfort, salivation, flushing of the skin (“hot feeling”), sweating, nausea, and vomiting.

Atropine Sulfate is a specific antidote. The recommended dose for adults is 0.6 mg. Repeat doses can be given every two hours, according to clinical response. The recommended dosage in infants and children up to 12 years of age is 0.01 mg/kg (to a maximum single dose of 0.4 mg) repeated every two hours as needed until the desired effect is obtained or adverse effects of atropine preclude further usage. Subcutaneous injection of atropine is preferred except in emergencies when the intravenous route may be employed.

The oral LD50 of bethanechol chloride is 1,510 mg/kg in the mouse.

DOSAGE AND ADMINISTRATION

Dosage must be individualized, depending on the type and severity of the condition to be treated.

Preferably give the drug when the stomach is empty. If taken soon after eating, nausea and vomiting may occur.

The usual adult oral dose ranges from 10 mg to 50 mg three or four times a day. The minimum effective dose is determined by giving 5 mg to 10 mg initially, and repeating the same amount at hourly intervals until satisfactory response occurs, or until a maximum of 50 mg has been given. The effects of the drug sometimes appear within 30 minutes, and are usually maximal within 60 to 90 minutes. The drug effects persist for about one hour.

If necessary, the effects of the drug can be abolished promptly by atropine (see OVERDOSAGE).

HOW SUPPLIED

Bethanechol Chloride Tablets, USP, 5 mg are supplied as white, round, flat faced, bevelled tablets debossed with ‘AN’ above bisect and ‘571’ below bisect on one side and plain on the other side.

They are available as follows:

Bottles of 100: NDC 53746-571-01

Bethanechol Chloride Tablets, USP, 10 mg are supplied as white, round, flat faced, bevelled tablets debossed with ‘AN’ above bisect and ‘572’ below bisect on one side and plain on the other side.

They are available as follows:

Bottles of 100: NDC 53746-572-01

Bethanechol Chloride Tablets, USP, 25 mg are supplied as yellow, round, flat faced, bevelled tablets debossed with ‘AN’ above bisect and ‘573’ below bisect on one side and plain on the other side.

They are available as follows:

Bottles of 100: NDC 53746-573-01

Bethanechol Chloride Tablets, USP, 50 mg are supplied as yellow, round, flat faced, bevelled tablets debossed with ‘AN’ above bisect and ‘574’ below bisect on one side and plain on the other side.

They are available as follows:

Bottles of 100: NDC 53746-574-01

Store at 20° to 25°C (68° to 77°F); excursions permitted between 15° to 30°C (59° to 86°F) [see USP Controlled Room Temperature].

This container is not intended for household use. Dispense in a tight, light-resistant container as defined in the USP, with a child-resistant closure (as required).

KEEP THIS AND ALL MEDICATIONS OUT OF THE REACH OF CHILDREN.

Manufactured by:
Amneal Pharmaceuticals Pvt. Ltd.
Oral Solid Dosage Unit
Ahmedabad 382213, INDIA

Distributed by:
Amneal Pharmaceuticals LLC
Bridgewater, NJ 08807

Rev.09-2021-00

PRINCIPAL DISPLAY PANEL

NDC 53746-571-01

Bethanechol Chloride Tablets, USP 5 mg

Amneal Pharmaceticals LLC

PRINCIPAL DISPLAY PANEL

NDC 53746-572-01

Bethanechol Chloride Tablets, USP 10 mg

Amneal Pharmaceticals LLC

PRINCIPAL DISPLAY PANEL

NDC 53746-573-01

Bethanechol Chloride Tablets, USP 25 mg

Amneal Pharmaceticals LLC

PRINCIPAL DISPLAY PANEL

NDC 53746-574-01

Bethanechol Chloride Tablets, USP 50 mg

Amneal Pharmaceticals LLC